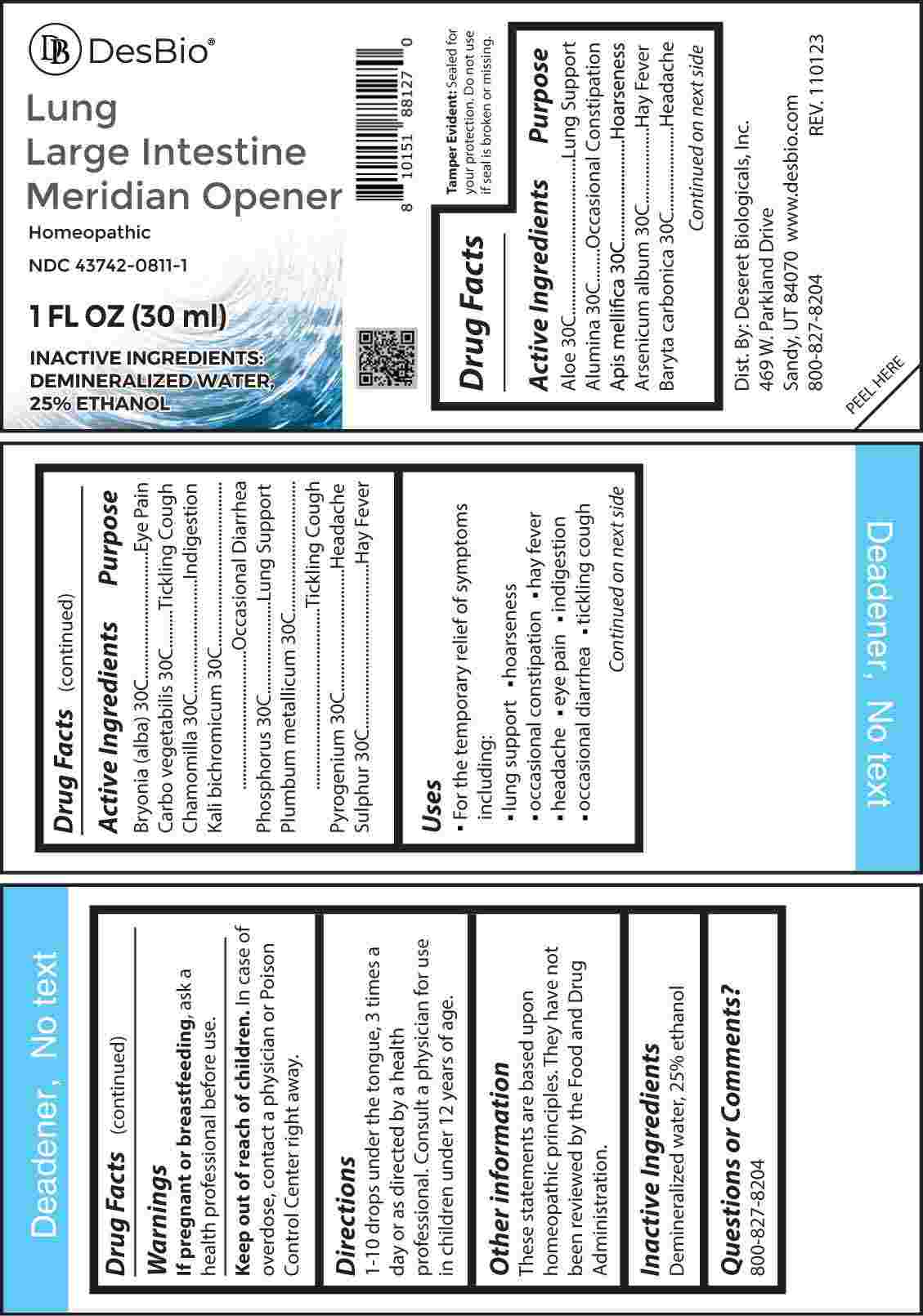 DRUG LABEL: Lung Large Intestine Meridian Opener
NDC: 43742-0811 | Form: LIQUID
Manufacturer: Deseret Biologicals, Inc
Category: homeopathic | Type: HUMAN OTC DRUG LABEL
Date: 20240221

ACTIVE INGREDIENTS: ALOE VERA LEAF 30 [hp_C]/1 mL; ALUMINUM OXIDE 30 [kp_C]/1 mL; APIS MELLIFERA 30 [hp_C]/1 mL; ARSENIC TRIOXIDE 30 [hp_C]/1 mL; BARIUM CARBONATE 30 [hp_C]/1 mL; BRYONIA ALBA ROOT 30 [hp_C]/1 mL; ACTIVATED CHARCOAL 30 [hp_C]/1 mL; MATRICARIA CHAMOMILLA WHOLE 30 [hp_C]/1 mL; POTASSIUM DICHROMATE 30 [hp_C]/1 mL; PHOSPHORUS 30 [hp_C]/1 mL; LEAD 30 [hp_C]/1 mL; RANCID BEEF 30 [hp_C]/1 mL; SULFUR 30 [hp_C]/1 mL
INACTIVE INGREDIENTS: WATER; ALCOHOL

DRUG FACTS:

ACTIVE INGREDIENTS:

Aloe 30C, Alumina 30C, Apis Mellifica 30C, Arsenicum Album 30C, Baryta Carbonica 30C, Bryonia (Alba) 30C, Carbo Vegetabilis 30C, Chamomilla 30C, Kali Bichromicum 30C, Phosphorus 30C, Plumbum Metallicum 30, Pyrogenium 30C, Sulphur 30C.

PURPOSE:

Aloe – Lung Support, Alumina – Occasional Constipation, Apis Mellifica - Hoarseness, Arsenicum Album – Hay Fever, Baryta Carbonica - Headache, Bryonia (Alba) - Eye Pain, Carbo Vegetabilis – Tickling Cough, Chamomilla - Indigestion, Kali Bichromicum – Occasional Diarrhea, Phosphorus – Lung Support, Plumbum Metallicum – Tickling Cough, Pyrogenium - Headache, Sulphur -Hay
Fever

USES:

• For the temporary relief of symptoms including:

• lung support • hoarseness • occasional constipation

• hay fever • headache • eye pain • indigestion

• occasional diarrhea • tickling cough

These statements are based upon homeopathic principles. They have not been reviewed by the Food and Drug Administration.

WARNINGS:

If pregnant or breast-feeding, ask a health professional before use.

Keep out of reach of children. In case of overdose, contact a physician or Poison Control Center right away.

Tamper Evident: Sealed for your protection. Do not use if seal is broken or missing.

KEEP OUT OF REACH OF CHILDREN:

In case of overdose, contact a physician or Poison Control Center right away.

DIRECTIONS:

1-10 drops under the tongue, 3 times a day or as directed by a health professional. Consult a physician for use in children under 12 years of age.

INACTIVE INGREDIENTS:

Demineralized water, 25% ethanol

QUESTIONS:

Dist. By: Deseret Biologicals, Inc.
469 W. Parkland Drive
Sandy, UT 84070

www.desbio.com

800-827-8204

PACKAGE LABEL DISPLAY:

Des Bio

Lung Large Intestine

Meridian Opener

Homeopathic

NDC 43742-0811-1

1 FL OZ (30 ml)